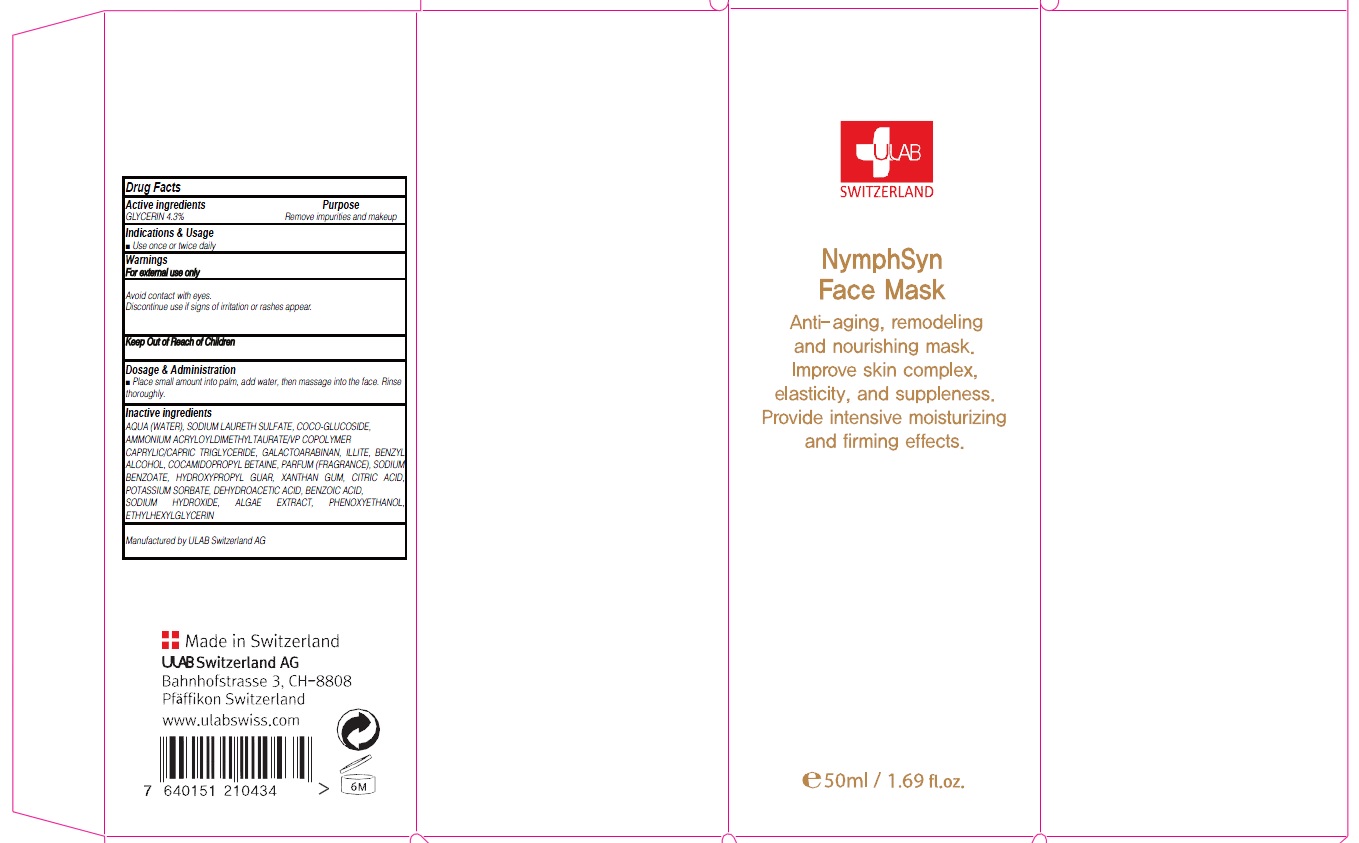 DRUG LABEL: NYMPHSYN FACE MASK
NDC: 71276-030 | Form: CREAM
Manufacturer: ULAB
Category: otc | Type: HUMAN OTC DRUG LABEL
Date: 20170321

ACTIVE INGREDIENTS: GLYCERIN 1.4 g/50 mL
INACTIVE INGREDIENTS: WATER; BUTYLENE GLYCOL

ACTIVE INGREDIENT

Active ingredients: GLYCERIN 2.8%

INACTIVE INGREDIENT

Inactive ingredients: AQUA (WATER), BUTYLENE GLYCOL, CAPRYLIC/CAPRIC TRIGLYCERIDE, COCO-CAPRYLATE/CAPRATE, C12-20 ACID PEG-8 ESTER, POTASSIUM CETYL PHOSPHATE, PHENOXYETHANOL, CI 77891 (TITANIUM DIOXIDE), CARBOMER, POLYACRYLAMIDE, SODIUM POTASSIUM ALUMINUM SILICATE, ETHYLHEXYLGLYCERIN, C13-14 ISOPARAFFIN, CHONDRUS CRISPUS POWDER (CARRAGEENAN), CARAMEL, SODIUM HYDROXIDE, MICA, PARFUM (FRAGRANCE), DISODIUM EDTA, SILICA, LAURETH-7, PEG-8, TRITICUM VULGARE (WHEAT) PROTEIN, PENTYLENE GLYCOL, SODIUM HYALURONATE, TETRADECYL AMINOBUTYROYLVALYLAMINOBUTYRIC UREA TRIFLUOROACETATE TOCOPHEROL, ASCORBYL PALMITATE, MAGNESIUM CHLORIDE, ASCORBIC ACID, CITRIC ACID, NICOTIANA SYLVESTRIS LEAF CELL CULTURE

PURPOSE

Purpose: Skin firming and remodeling

WARNINGS

Warnings: For external use only Avoid contact with eyes. Discontinue use if signs of irritation or rashes appear.

KEEP OUT OF REACH OF CHILDREN

INDICATIONS & USAGE

Indications & Usage: Use one to three times a week

DOSAGE & ADMINISTRATION

Dosage & Administration: - Apply a generous, even layer to clean skin - Leave on for 5 to 10 minutes, then wash-off or leave on over-night